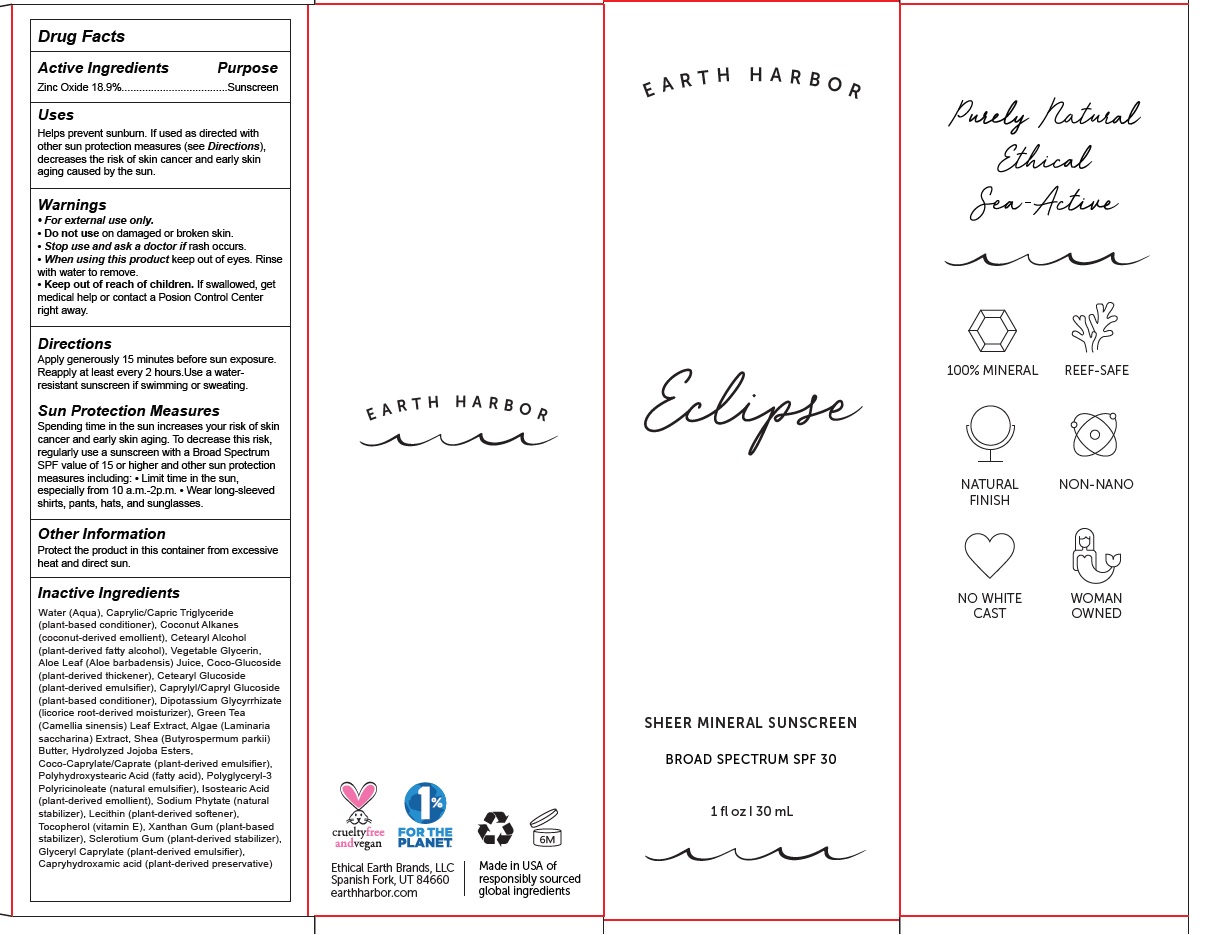 DRUG LABEL: Eclipse Sheer Mineral Sunscreen Broad Spectrum SPF 30
NDC: 62742-4204 | Form: CREAM
Manufacturer: Allure Labs
Category: otc | Type: HUMAN OTC DRUG LABEL
Date: 20210503

ACTIVE INGREDIENTS: ZINC OXIDE 189 mg/1 mL
INACTIVE INGREDIENTS: COCONUT ALKANES; POLYGLYCERYL-3 PENTARICINOLEATE; ISOSTEARIC ACID; TOCOPHEROL; GLYCERYL CAPRYLATE; CAPRYLHYDROXAMIC ACID; GREEN TEA LEAF; POLYHYDROXYSTEARIC ACID STEARATE; LECITHIN, SOYBEAN; XANTHAN GUM; ALOE; GLYCYRRHIZINATE DIPOTASSIUM; SACCHARINA LATISSIMA; SHEA BUTTER; CETOSTEARYL ALCOHOL; GLYCERIN; COCO GLUCOSIDE; CETEARYL GLUCOSIDE; MEDIUM-CHAIN TRIGLYCERIDES; WATER; CAPRYLYL/CAPRYL OLIGOGLUCOSIDE; HYDROLYZED JOJOBA ESTERS (ACID FORM); COCO-CAPRYLATE/CAPRATE; PHYTATE SODIUM; BETASIZOFIRAN

Drug Facts

Active Ingredients

Zinc Oxide 18.9%

Purpose: Sunscreen

Uses
Helps prevent sunburn. If used as directed with other sun protection measures (see Directions), decreases the risk of skin cancer and early skin aging caused by the sun.

Warnings
• For external use only.

Do Not use on damaged or broken skin.

Stop use and ask a doctor if rash occurs.

When using this product keep out of eyes. Rinse with water to remove.

Keep out of reach of children. If swallowed, get medical help or contact a Posion Control Center right away.

Directions
Apply generously 15 minutes before sun exposure. Reapply at least every 2 hours.Use a waterresistant sunscreen if swimming or sweating.

Other Information
Protect the product in this container from excessive heat and direct sun.

INACTIVE INGREDIENT

Water (Aqua), Caprylic/Capric Triglyceride (plant-based conditioner), Coconut Alkanes (coconut-derived emollient), Cetearyl Alcohol (plant-derived fatty alcohol), Vegetable Glycerin, Aloe Leaf (Aloe barbadensis) Juice, Coco-Glucoside (plant-derived thickener), Cetearyl Glucoside (plant-derived emulsifier), Caprylyl/Capryl Glucoside (plant-based conditioner), Dipotassium Glycyrrhizate (licorice root-derived moisturizer), Green Tea (Camellia sinensis) Leaf Extract, Algae (Laminaria saccharina) Extract, Shea (Butyrospermum parkii) Butter, Hydrolyzed Jojoba Esters, Coco-Caprylate/Caprate (plant-derived emulsifier), Polyhydroxystearic Acid (fatty acid), Polyglyceryl-3 Polyricinoleate (natural emulsifier), Isostearic Acid (plant-derived emollient), Sodium Phytate (natural stabilizer), Lecithin (plant-derived softener), Tocopherol (vitamin E), Xanthan Gum (plant-based stabilizer), Sclerotium Gum (plant-derived stabilizer), Glyceryl Caprylate (plant-derived emulsifier), Capryhydroxamic acid (plant-derived preservative)

PACKAGE LABEL

Ethical Earth Brands, LLC
Spanish Fork, UT 84660
earthharbor.com

Made in USA of responsibly sourced global ingredients